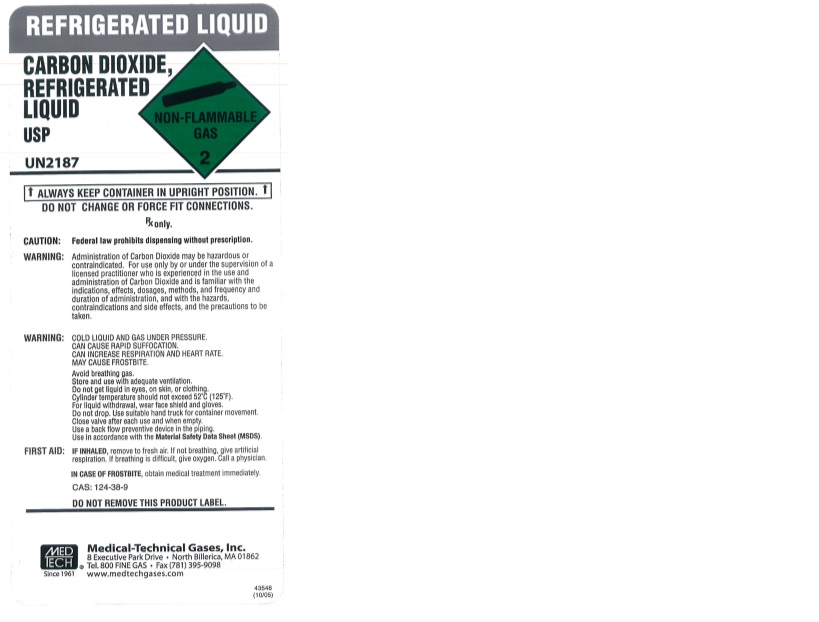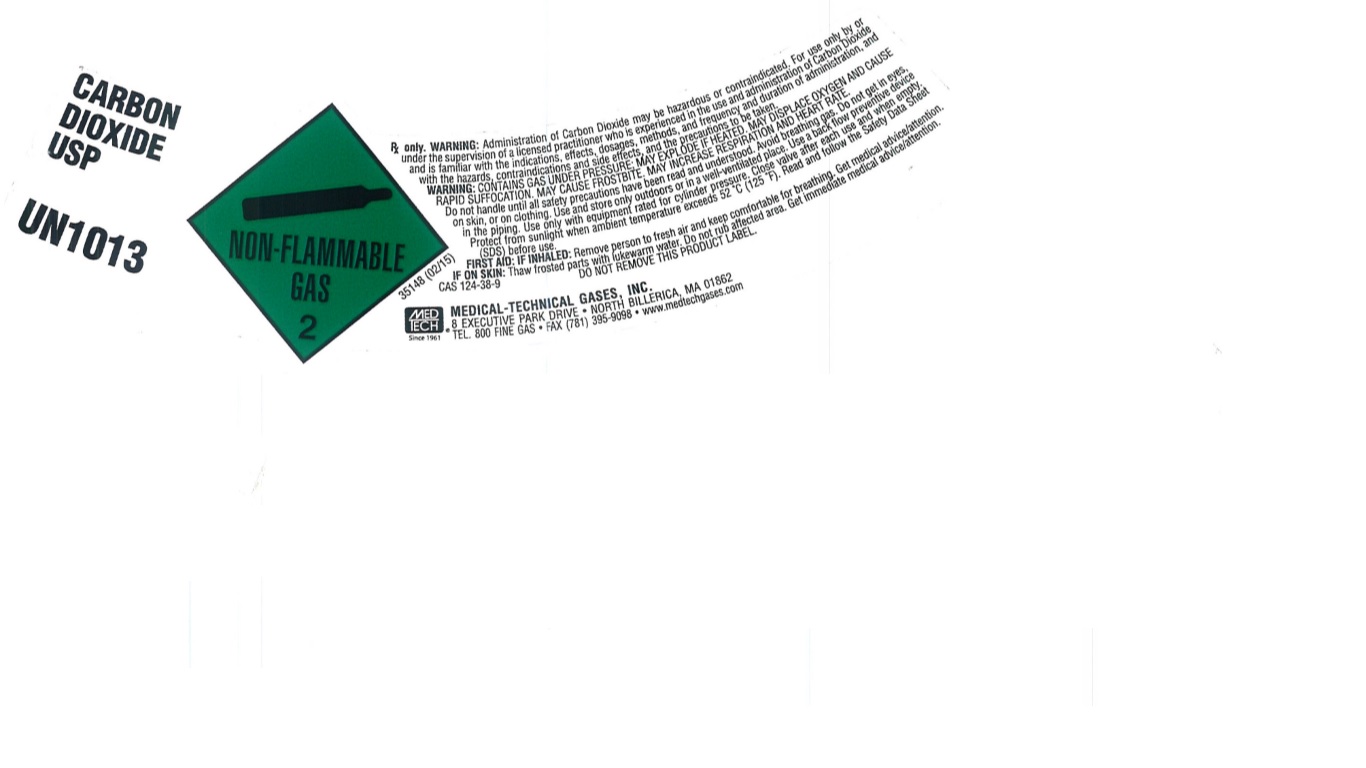 DRUG LABEL: Carbon Dioxide
NDC: 10736-014 | Form: GAS
Manufacturer: MEDICAL-TECHNICAL GASES, INC.
Category: prescription | Type: HUMAN PRESCRIPTION DRUG LABEL
Date: 20251125

ACTIVE INGREDIENTS: CARBON DIOXIDE 995 mL/1 L

Carbon Dioxide Label

PACKAGE LABEL

REFRIGERATED LIQUID
CARBON DIOXIDE, REFRIGERATED LIQUID
USP
UN2187
ALWAYS KEEP CONTAINER IN UPRIGHT POSITION.
DO NOT CHANGE OR FORCE FIT CONNECTIONS.
Rx only.
CAUTION: Federal law prohibits dispensing without prescription.
WARNING: Administration of Carbon Dioxide may be hazardous or contraindicated. For use only by or under the supervision of a licensed practitioner who is experienced in the use and administration of Carbon Dioxide and is familiar with the indications, effects, dosages, methods, and frequency and duration of administration, and with the hazards, contraindications and side effects, and the precautions to be taken.
WARNING: COLD LIQUID AND GAS UNDER PRESSURE.
CAN CAUSE RAPID SUFFOCATION.
CAN INCREASE RESPIRATION AND HEART RATE.
MAY CAUSE FROSTBITE.
Avoid breathing gas.
Store and use with adequate ventilation.
Do not get liquid in eyes, on skin, or clothing.
Cylinder temperature should not exceed 52 C (125 F).
For liquid withdrawal, wear face shield and gloves.
Do not drop. Use suitable hand truck for container movement.
Close valve after each use and when empty.
Use a back flow preventive device in the piping.
Use in accordance with the Material Safety Data Sheet (MSDS).
FIRST AID: IF INHALED, remove to fresh air. If not breathing give artificial respiration. If breathing is difficult, give oxygen. Call a physician.
IN CASE OF FROSTBITE, obtain medical treatment immediately.
CAS: 124-38-9

DO NOT REMOVE THIS PRODUCT LABEL.
MEDTECH Since 1961
MEDICAL-TECHNICAL GASES, INC.
8 EXECUTIVE PARK DRIVE NORTH BILLERICA, MA 01862
TEL. 800 FINE GAS FAX (781) 395-9098 www.medtechgases.com

PACKAGE LABEL

CARBON DIOXIDE USP
UN1013
Rx only. WARNING: Administration of Carbon Dioxide may be hazardous or contraindicated. For use only by or under the supervision of a licensed practitioner who is experienced in the use and administration of Carbon Dioxide and is familiar with the indications, effects, dosages, methods, and frequency and duration of administration, and with the hazards, contraindications and side effects, and the precautions to be taken.
WARNING: CONTAINS GAS UNDER PRESSURE; MAY EXPLODE IF HEATED. MAY DISPLACE OXYGEN AND CAUSE RAPID SUFFOCATION. MAY CAUSE FROSTBITE. MAY INCREASE RESPIRATION AND HEART RATE.
Do not handle until all safety precautions have been read and understood. Avoid breathing gas. Do not get in eyes, on skin, or on clothing. Use and store only outdoors or in a well-ventilated place. Use a back flow preventive device in the piping. Use only with equipment rated for cylinder pressure. Close valve after each use and when empty. Protect from sunlight when ambient temperature exceeds 52 C (125 F). Read and follow the Safety Data Sheet (SDS) before use.
FIRST AID: IF INHALED: Remove person to fresh air and keep comfortable for breathing. Get medical advice/attention. IF ON SKIN: Thaw frosted parts with lukewarm water. Do not rub affected area. Get immediate medical advice/attention.
CAS 124-38-9 DO NOT REMOVE THIS PRODUCT LABEL.
MEDTECH Since 1961
MEDICAL-TECHNICAL GASES, INC.
8 EXECUTIVE PARK DRIVE NORTH BILLERICA, MA 01862
TEL. 800 FINE GAS FAX (781) 395-9098 www.medtechgases.com